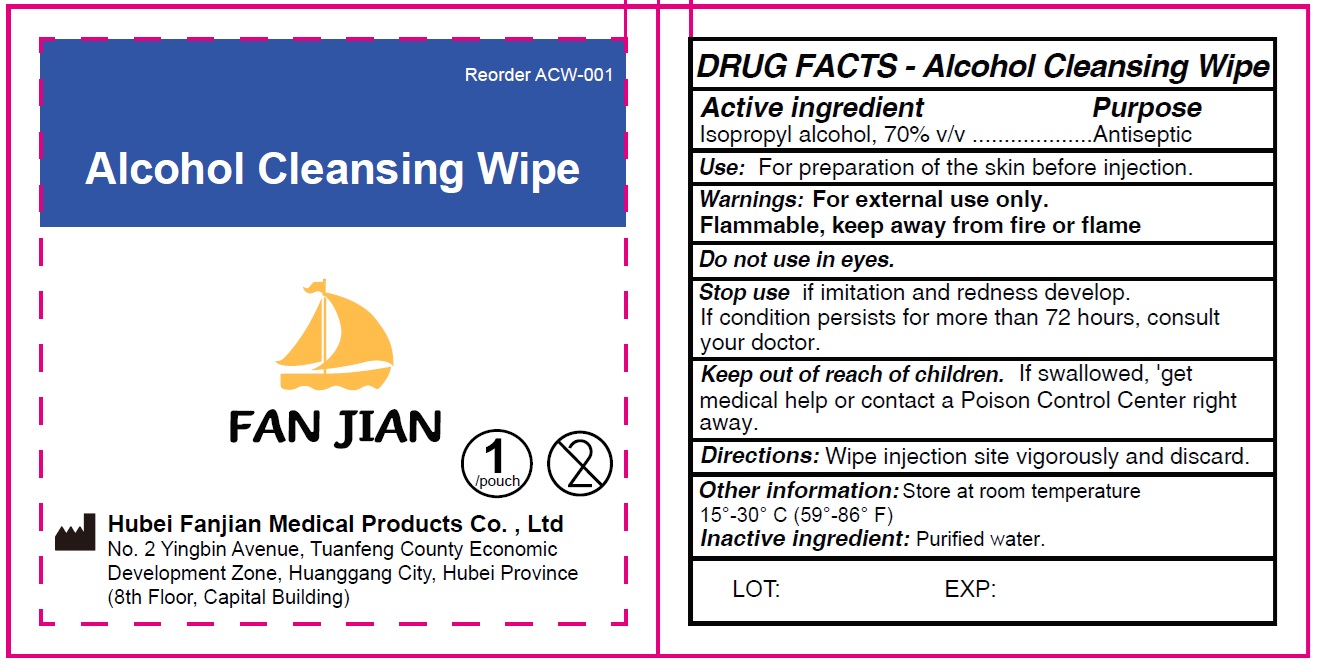 DRUG LABEL: Alcohol Cleansing Wipe
NDC: 83165-006 | Form: CLOTH
Manufacturer: Hubei Fanjian Medical Product Co.,Ltd
Category: otc | Type: HUMAN OTC DRUG LABEL
Date: 20250411

ACTIVE INGREDIENTS: ISOPROPYL ALCOHOL 70 mL/100 mL
INACTIVE INGREDIENTS: WATER

Alcohol Cleansing Wipe

Active ingredient

Isopropyl alcohol, 70% v/v

Purpose

Antiseptic

Use:

For preparation of the skin before injection.

Warnings:

For external use only.

Flammable, keep away from fire or flame

Do not use

in eyes.

Stop use if

imitation and redness develop. If condition persists for more than 72 hours, consult your doctor.

Keep out of reach of children.

If swallowed, 'get medical help or contact a Poison Control Center right away.

Directions:

Wipe injection site vigorously and discard.

Other information:

Store at room temperature 15°-30° C (59°-86° F)

Inactive ingredient:

Purified water.